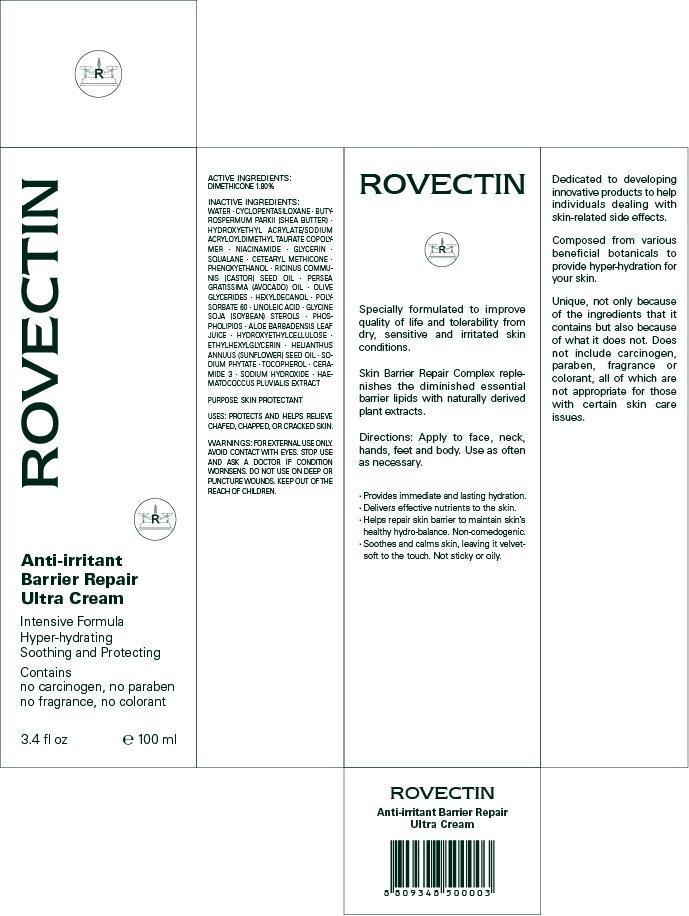 DRUG LABEL: ROVECTIN
NDC: 52970-010 | Form: CREAM
Manufacturer: SECOND FORMULA INC.
Category: otc | Type: HUMAN OTC DRUG LABEL
Date: 20120904

ACTIVE INGREDIENTS: Dimethicone 1.8 g/100 mL
INACTIVE INGREDIENTS: Water; Shea Butter; Niacinamide; Glycerin; Squalane

ACTIVE INGREDIENT

ACTIVE INGREDIENT: DIMETHICONE 1.80%

INACTIVE INGREDIENT

INACTIVE INGREDIENTS:
WATER, CYCLOPENTASILOXANE, BUTYROSPERMUM PARKII (SHEA BUTTER), HYDROXYETHYL ACRYLATE/SODIUM ACRYLOYLDIMETHYL TAURATE COPOLYMER, NIACINAMIDE, GLYCERIN, SQUALANE, CETEARYL METHICONE, PHENOXYETHANOL, RICINUS COMMUNIS (CASTOR) SEED OIL, PERSEA GRATISSIMA (AVOCADO) OIL, OLIVE GLYCERIDES, HEXYLDECANOL, POLYSORBATE 60, LINOLEIC ACID, GLYCINE SOJA (SOYBEAN) STEROLS, PHOSPHOLIPIDS, ALOE BARBADENSIS LEAF JUICE, HYDROXYETHYLCELLULOSE, ETHYLHEXYLGLYCERIN, HELIANTHUS ANNUUS (SUNFLOWER) SEED OIL, SODIUM PHYTATE, TOCOPHEROL, CERAMIDE 3, SODIUM HYDROXIDE, HAEMATOCOCCUS PLUVIALIS EXTRACT

PURPOSE

PURPOSE: SKIN PROTECTANT

WARNINGS

FOR EXTERNAL USE ONLY.
AVOID CONTACT WITH EYES.
STOP USE AND ASK A DOCTOR IF CONDITION WORNSENS.
DO NOT USE ON DEEP OR PUNCTURE WOUNDS.
KEEP OUT OF THE REACH OF CHILDREN.

KEEP OUT OF REACH OF CHILDREN

INDICATIONS AND USAGE

Directions:
Apply to face, neck, hands, feet and body.
Use as often as necessary.

DOSAGE AND ADMINISTRATION

Directions:
Apply to face, neck, hands, feet and body.
Use as often as necessary.